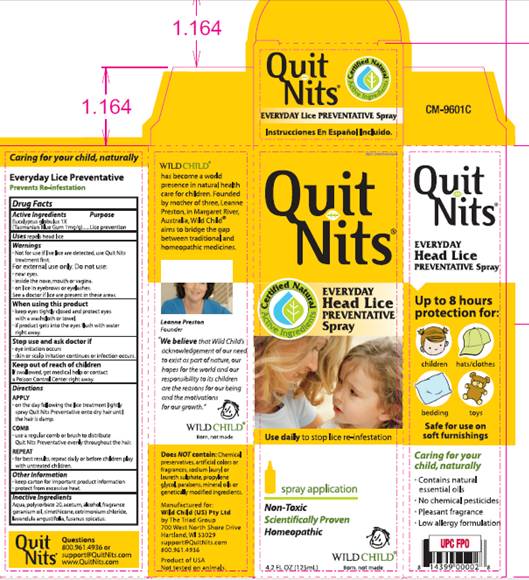 DRUG LABEL: Quit Nits Preventative
NDC: 30807-3003 | Form: SPRAY
Manufacturer: Wild Child W A Pty Ltd
Category: homeopathic | Type: HUMAN OTC DRUG LABEL
Date: 20091028

ACTIVE INGREDIENTS: eucalyptus globulus leaf 1 [HP_X]/125 mL
INACTIVE INGREDIENTS: water; polysorbate 20; acetic acid; alcohol; dimethicone; cetrimonium chloride

DRUG FACTS

ACTIVE INGREDIENTS

Eucalyptus globulus 1X (Tasmanian Blue Gum 1mg/g)

PURPOSE

Lice prevention

USE

repels head lice

WARNINGS

Not for use if live lice are detected, use Quit Nits treatment first.

For external use only.

DO NOT USE

- near eyes
- inside the nose, mouth or vagina
- on lice in eyebrows or eyelashes

See a doctor if lice are present in these areas.

WHEN USING THIS PRODUCT

- keep tightly closed and protect eyes with a washcloth or towel.
- if product gets into the eyes, flush with water right away.

STOP USE AND ASK A DOCTOR IF

- eye irritation occurs
- skin or scalp irritation continues or infection occurs

KEEP OUT OF REACH OF CHILDREN

If swallowed, get medical help or contact a Poison Control Center right away.

DIRECTIONS

Apply
On the day following the lice treatment lightly spray Quit Nits Preventative onto dry hair until the hair is damp
Comb
Use a regular comb or brush to distribute Quit Nits Preventative evenly throughout the hair
Repeat
For best results, repeat daily or before children play with untreated children

OTHER INFORMATION

- keep carton for important product information
- protect from excessive heat

INACTIVE INGREDIENTS

aqua, polysorbate 20, acetum, alcohol, fragrance, geranium oil, simethicone, cetrimonium chloride, lavandula angustifolia, fusanus spicatus

QUESTIONS

800-961-4936 or

support@QuitNits.com

www.QuitNits.com

PACKAGING INFORMATION

Quit Nits®
Homeopathic Everyday Head Lice Preventative Spray
Certified Natural Active Ingredients
Use daily to stop lice re-infestation
Spray application
Non-toxic
Scientifically Proven
Homeopathic
WILD CHILD®
Born, not made.
4.2 FL. OZ (125 ml)
Up to 8 hours protection for

- children
- hats/clothes
- bedding
- toys

Caring for your child, naturally

- Contains natural essential oils
- No chemical pesticides
- Pleasant fragrance
- Low allergy formulation

WILD CHILD® has become a world presence in natural health care for children. Founded by mother of three, Leanne Preston, in Margaret River, Australia, Wild Child aims to bridge the gap between traditional and homeopathic medicines.
Leanne Preston, Founder
"We believe that Wild Child's acknowledgment of our need to exist as part of nature, our hopes for the world and our responsibility to its children are the reasons for our being and the motivations for our growth."
WILD CHILD®
Born, not made.
Does NOT Contain: Chemical preservatives, artificial colors or fragrances, sodium lauryl or laureth sulfate, propylene glycol, parabens, mineral oils or genetically modified ingredients.
Manufactured for:
Wild Child (US) Pty Ltd
by The Triad Group
700 West North Shore Drive
Hartland, WI 53029
support@QuitNits.com
800.961.4936
Product of USA
Not tested on animals.